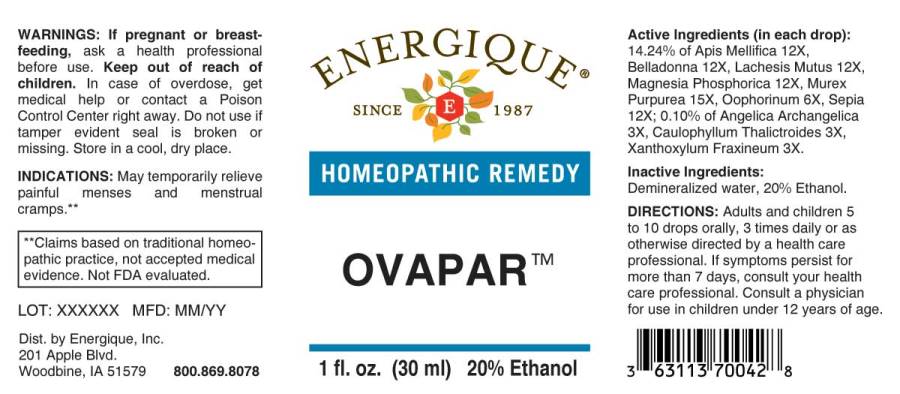 DRUG LABEL: Ovapar
NDC: 44911-0326 | Form: LIQUID
Manufacturer: Energique, Inc.
Category: homeopathic | Type: HUMAN OTC DRUG LABEL
Date: 20241029

ACTIVE INGREDIENTS: ANGELICA ARCHANGELICA ROOT 3 [hp_X]/1 mL; CAULOPHYLLUM THALICTROIDES ROOT 3 [hp_X]/1 mL; ZANTHOXYLUM AMERICANUM BARK 3 [hp_X]/1 mL; SUS SCROFA OVARY 6 [hp_X]/1 mL; APIS MELLIFERA 12 [hp_X]/1 mL; ATROPA BELLADONNA 12 [hp_X]/1 mL; LACHESIS MUTA VENOM 12 [hp_X]/1 mL; MAGNESIUM PHOSPHATE, DIBASIC TRIHYDRATE 12 [hp_X]/1 mL; SEPIA OFFICINALIS JUICE 12 [hp_X]/1 mL; HEXAPLEX TRUNCULUS HYPOBRANCHIAL GLAND JUICE 15 [hp_X]/1 mL
INACTIVE INGREDIENTS: WATER; ALCOHOL

DRUG FACTS:

ACTIVE INGREDIENTS:

(in each drop): 14.24% of Apis Mellifica 12X, Belladonna 12X, Lachesis Mutus 12X, Magnesia Phosphorica 12X, Murex Purpurea 15X, Oophorinum (Suis) 6X, Sepia 12X; 0.10% of Angelica Archangelica 3X, Caulophyllum Thalictroides 3X, Xanthoxylum Fraxineum 3X.

INDICATIONS:

May temporarily relieve painful menses and menstrual cramps.**

**Claims based on traditional homeopathic practice, not accepted medical evidence. Not FDA evaluated.

WARNINGS:

If pregnant or breastfeeding, ask a health professional before use.

Keep out of reach of children. In case of overdose, get medical help or contact a Poison Control Center right away.

Do not use if tamper evident seal is broken or missing.

Store in a cool, dry place.

Keep out of reach of children. In case of overdose, get medical help or contact a Poison Control Center right away.

DIRECTIONS:

Adults and children 5 to 10 drops orally, 3 times daily or as otherwise directed by a health care professional. If symptoms persist for more than 7 days, consult your health care professional. Consult a physician for use in children under 12 years of age.

INDICATIONS:

May temporarily relieve painful menses and menstrual cramps.**

**Claims based on traditional homeopathic practice, not accepted medical evidence. Not FDA evaluated.

INACTIVE INGREDIENTS:

Demineralized water, 20% Ethanol.

QUESTIONS:

Dist. by Energique, Inc.
201 Apple Blvd.
Woodbine, IA 51579 800.869.8078

PACKAGE LABEL DISPLAY:

ENERGIQUE

SINCE 1987

HOMEOPATHIC REMEDY

OVAPAR

1 fl. oz. (30 ml)